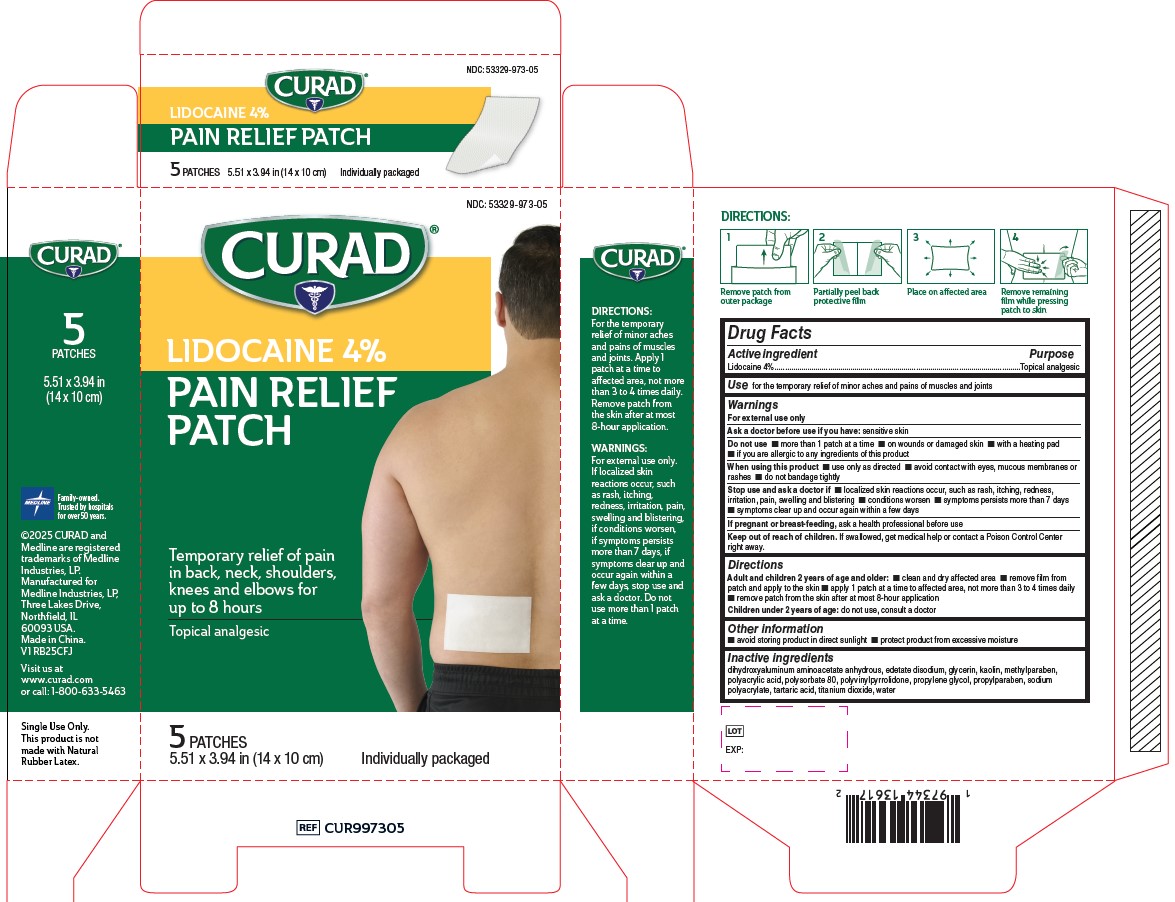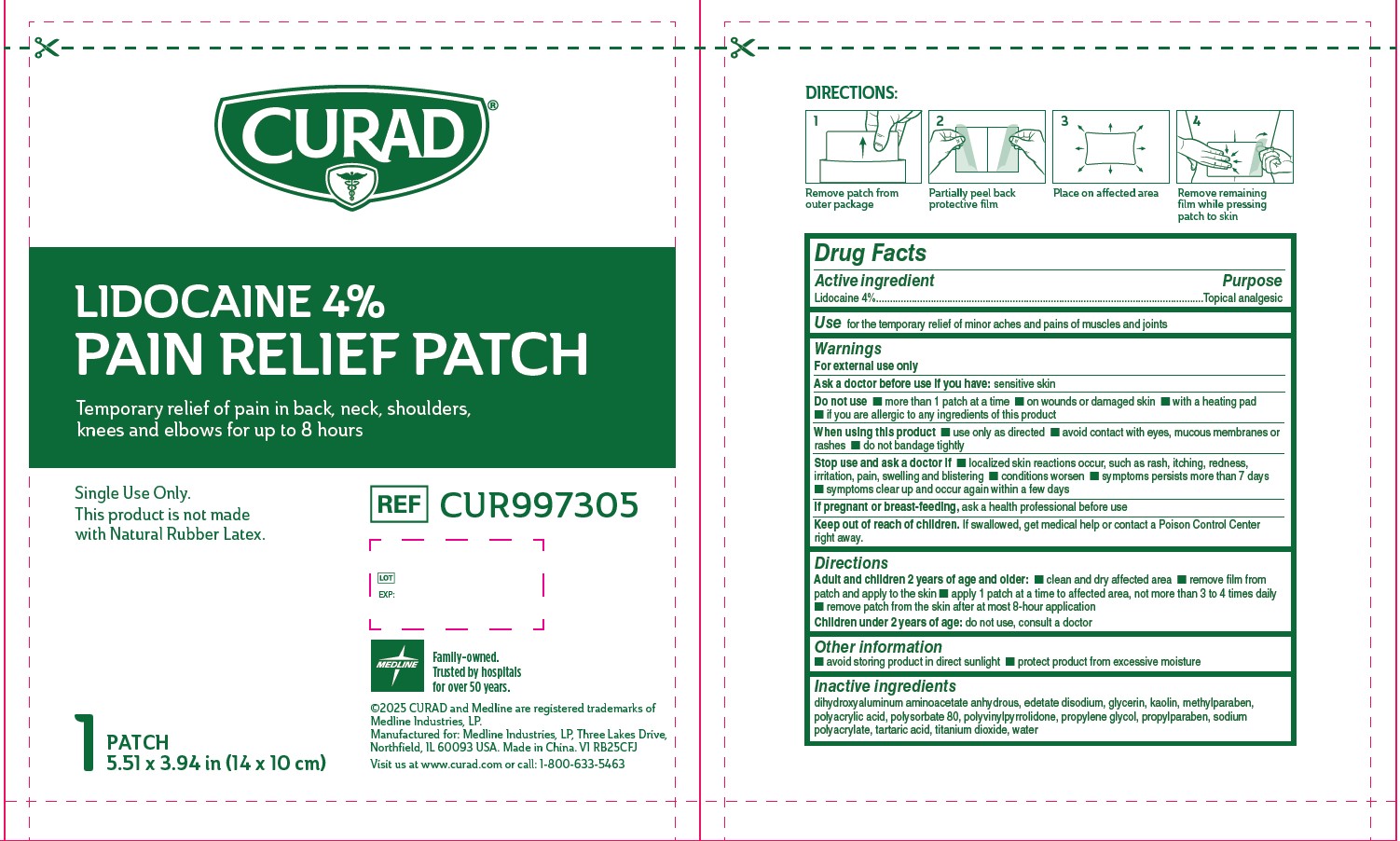 DRUG LABEL: Medline
NDC: 53329-973 | Form: PATCH
Manufacturer: Medline Industries, LP
Category: otc | Type: HUMAN OTC DRUG LABEL
Date: 20250626

ACTIVE INGREDIENTS: LIDOCAINE 4 mg/100 mg
INACTIVE INGREDIENTS: METHYLPARABEN; PROPYLENE GLYCOL; POLYSORBATE 80; TARTARIC ACID; DIHYDROXYALUMINUM AMINOACETATE ANHYDROUS; KAOLIN; POLYACRYLIC ACID (250000 MW); WATER; GLYCERIN; TITANIUM DIOXIDE; SODIUM POLYACRYLATE (2500000 MW); EDETATE DISODIUM; POVIDONE, UNSPECIFIED; PROPYLPARABEN

973 Medline 4% Lidocain Pain Relief Patch

Active ingredient

Lidocaine 4%

Purpose

Topical analgesic

Use

for the temporary relief of minor aches and pains of muscles and joints

Warnings

For external use only

Ask doctor before use if you have:

sensitive skin

Do not use

- more than 1 patch at a time
- on wounds or damaged skin
- with a heating pad
- if you are allergic to any ingredients of this product

When using this product

- use only as directed
- avoid contact with eyes, mucous membranes or rashes
- do not bandage tightly

Stop use and ask a doctor if

- localized skin reactions occur, such as rash, itching, redness, irritation, pain, swelling and blistering
- conditions worsen
- symptoms persists more than 7 days
- symptoms clear up and occur again within a few days

If pregnant of breast-feeding,

ask a health professional before use

Keep out of reach of children.

If swallowed, get medical help or contact a Poison Control Center right away.

Directions

Adult and children 2 years of age and older:

- clean and dry affected area
- remove film from patch and apply to the skin
- apply 1 patch at a time to affected area, not more than 3 to 4 times daily
- remove patch from the skin after at most 8-hour application

Children under 2 years of age: do not use, consult a doctor

Other information

- avoid storing product in direct sunlight
- protect product from excessive moisture

Inactive ingredients

dihydroxyaluminum aminoacetate anhydrous, edetate disodium, glycerin, kaolin, methylparaben, polyacrylic acid, polysorbate 80, polyvinylpyrrolidone, propylene glycol, propylparaben, sodium polyacrylate, tartaric acid, titanium dioxide, water

Manufacturer information

©2025 CURAD and Medline are registered trademarks of Medline Industries, LP.
Manufactured for Medline Industries, LP,
Three Lakes Drive, Northfield, IL 60093 USA.
Made in China.

REF CUR997305 V1 RB25CFJ